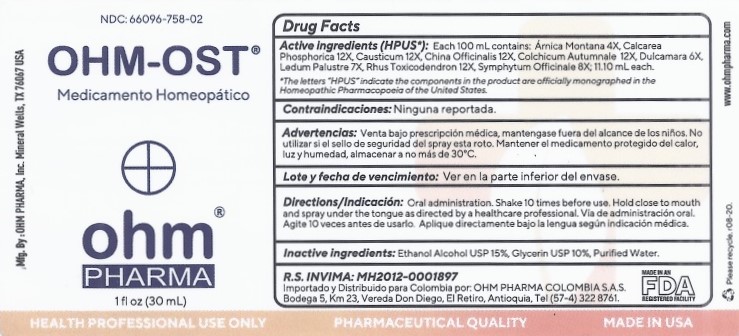 DRUG LABEL: OHM-OST
NDC: 66096-758 | Form: SPRAY
Manufacturer: OHM PHARMA INC.
Category: homeopathic | Type: HUMAN PRESCRIPTION DRUG LABEL
Date: 20210325

ACTIVE INGREDIENTS: ARNICA MONTANA 4 [hp_X]/30 mL; TRIBASIC CALCIUM PHOSPHATE 12 [hp_X]/30 mL; CAUSTICUM 12 [hp_X]/30 mL; CINCHONA OFFICINALIS BARK 12 [hp_X]/30 mL; COLCHICUM AUTUMNALE BULB 12 [hp_X]/30 mL; SOLANUM DULCAMARA TOP 6 [hp_X]/30 mL; LEDUM PALUSTRE TWIG 7 [hp_X]/30 mL; TOXICODENDRON PUBESCENS LEAF 12 [hp_X]/30 mL; COMFREY ROOT 8 [hp_X]/30 mL
INACTIVE INGREDIENTS: ALCOHOL; GLYCERIN; WATER

OHM-OST

ACTIVE INGREDIENT

Active ingredients (HPUS*): 100 mL contains: Arnica Montana 4X, Calcarea Phosphorica 12X, Causticum 12X, China Officinalis 12X,

Colchicum Autumnale 12X, Dulcamara 6X, Ledum Palustre 7X, Rhus Toxicodendron 12X, Symphytum Officianale 8X; 11.10 mL each.

*The letters "HPUS" indicate the components in the product are officially monographed in the Homeopathic Pharmacopoeia of the United States.

INDICATIONS AND USAGE

Contraindicaciones: Ninguna reportada

WARNINGS

Advertencias: Venta bajo prescripción médica, mantengase fuera del alcance de los niños. No utilizar si el sello de seguridad del spray esta roto. Mantener el medicamento protegido del calor, luz y humedad, almacenar a no más de 30°C.

KEEP OUT OF REACH OF CHILDREN

Mantengase fuera del alcance de los niños.

DOSAGE AND ADMINISTRATION

Directions / Indicacion:Oral administration. Shake 10 times before use. Hold close to mouth and spray under the tongue as directed by a healthcare professional. Via de administracion oral. Agite 10 veces antes de usarlo. Aplique directamente bajo la lengua segun indicacion medica.

OTHER SAFETY INFORMATION

Lote y fecha de vencimiento: Ver en la parte inferior del envase

INACTIVE INGREDIENT

Inactive ingredients:Ethanol Alcohol USP 15%, Glycerin USP 10%, Purified Water.

QUESTIONS

R.S. INVIMA: MH2010-0001591
Importado y Distribuido para Colombia por: OHM PHARMA COLOMBIA S.A.S.
Bodega 5, Km 23, Vereda Don Diego, El Retiro, Antioquia, Tel (57-4) 322 8761.

Mfg. By : OHM PHARMA, Inc.
Mineral Wells, TX 76067 USA
www.ohmpharma.com

PACKAGE LABEL

NDC: 66096-758-02

OHM-OST

Medicamiento Homeopatico

PURPOSE

Medicamento Homeopatico